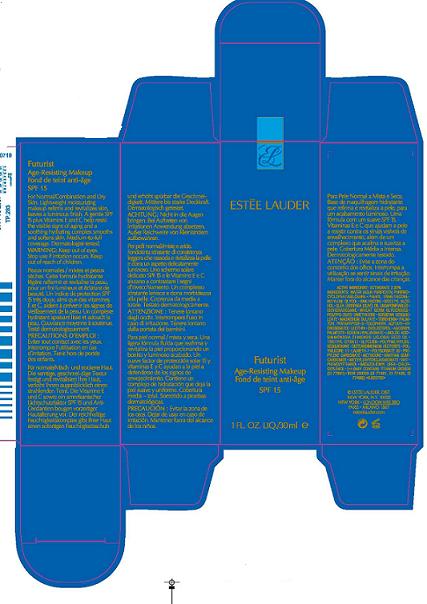 DRUG LABEL: FUTURIST AGE RESISTING MAKEUP
NDC: 11559-003 | Form: LIQUID
Manufacturer: ESTEE LAUDER INC
Category: otc | Type: HUMAN OTC DRUG LABEL
Date: 20100406

ACTIVE INGREDIENTS: OCTINOXATE 2.20 mL/100 mL

ACTIVE INGREDIENT: OCTINOXATE 2.2%

WARNINGS

WARNING: KEEP OUT OF EYES. STOP USE IF IRRITATION OCCURS.

KEEP OUT OF REACH OF CHILDREN

PACKAGE LABEL

PRINCIPAL DISPLAY PANEL

ESTEE LAUDER

FUTURIST

AGE-RESISTING MAKEUP

SPF 15

1 FL 0Z / 30 ML

ESTEE LAUDER DIST

NEW YORK, NY 10022